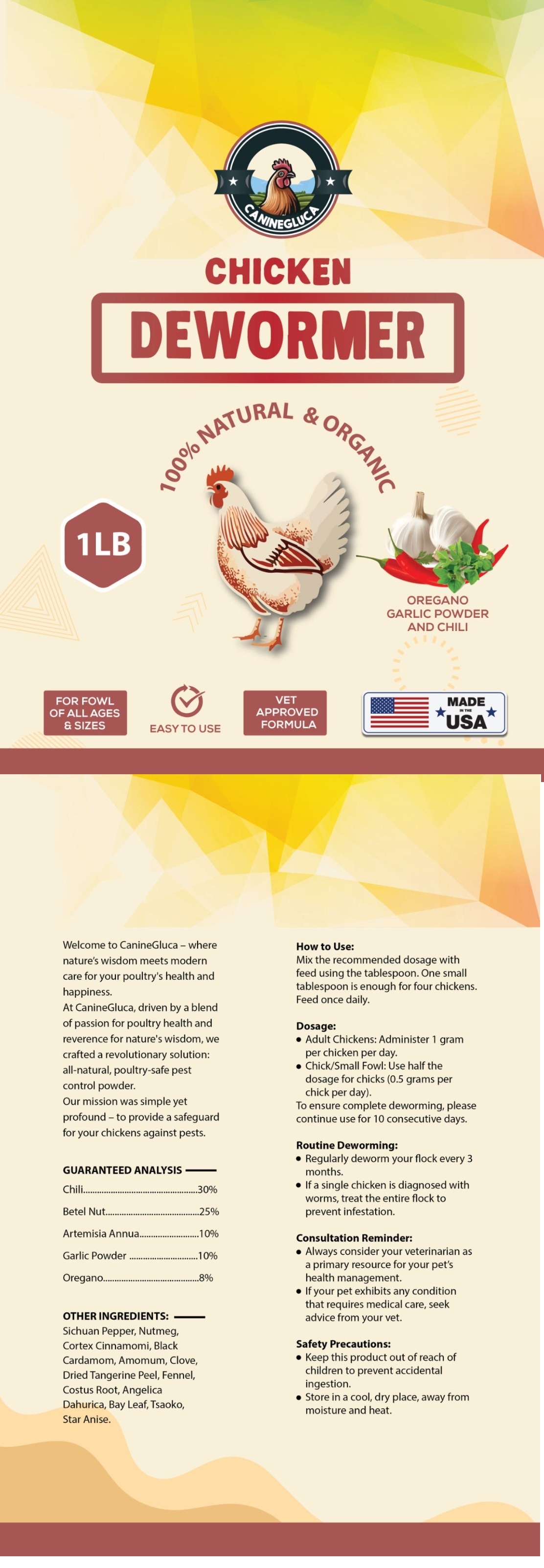 DRUG LABEL: Chicken Dewormer
NDC: 86202-0243 | Form: TABLET
Manufacturer: AMBIENCE FAMILY INC
Category: animal | Type: OTC ANIMAL DRUG LABEL
Date: 20240708

ACTIVE INGREDIENTS: CHILIPEPPER ROCKFISH, COOKED 135 g/1 g; ARTEMISIA ANNUA POLLEN 45 g/1 g; GARLIC 45 g/1 g; OREGANO 36 g/1 g
INACTIVE INGREDIENTS: NUTMEG; CARDAMOM; AMOMUM SUBULATUM FRUIT; TANGERINE PEEL; ANGELICA DAHURICA ROOT; BAY LEAF; ANISE

Chicken Dewormer 100% Organic

WARNINGS AND PRECAUTIONS

Not for use in humans. Keep out of reach of children. Protective gloves should be used and care should be taken when handling the product to avoid skin and eye exposure and accidental ingestion. Accidental exposure may result in skin and eye irritation. Accidental ingestion may cause gastrointestinal disturbances and hypersensitivity reactions in humans.

WARNINGS AND PRECAUTIONS

Not for use in humans. Keep out of reach of children. Protective gloves should be used and care should be taken when handling the product to avoid skin and eye exposure and accidental ingestion. Accidental exposure may result in skin and eye irritation. Accidental ingestion may cause gastrointestinal disturbances and hypersensitivity reactions in humans.

PACKAGE LABEL

Content of Labeling